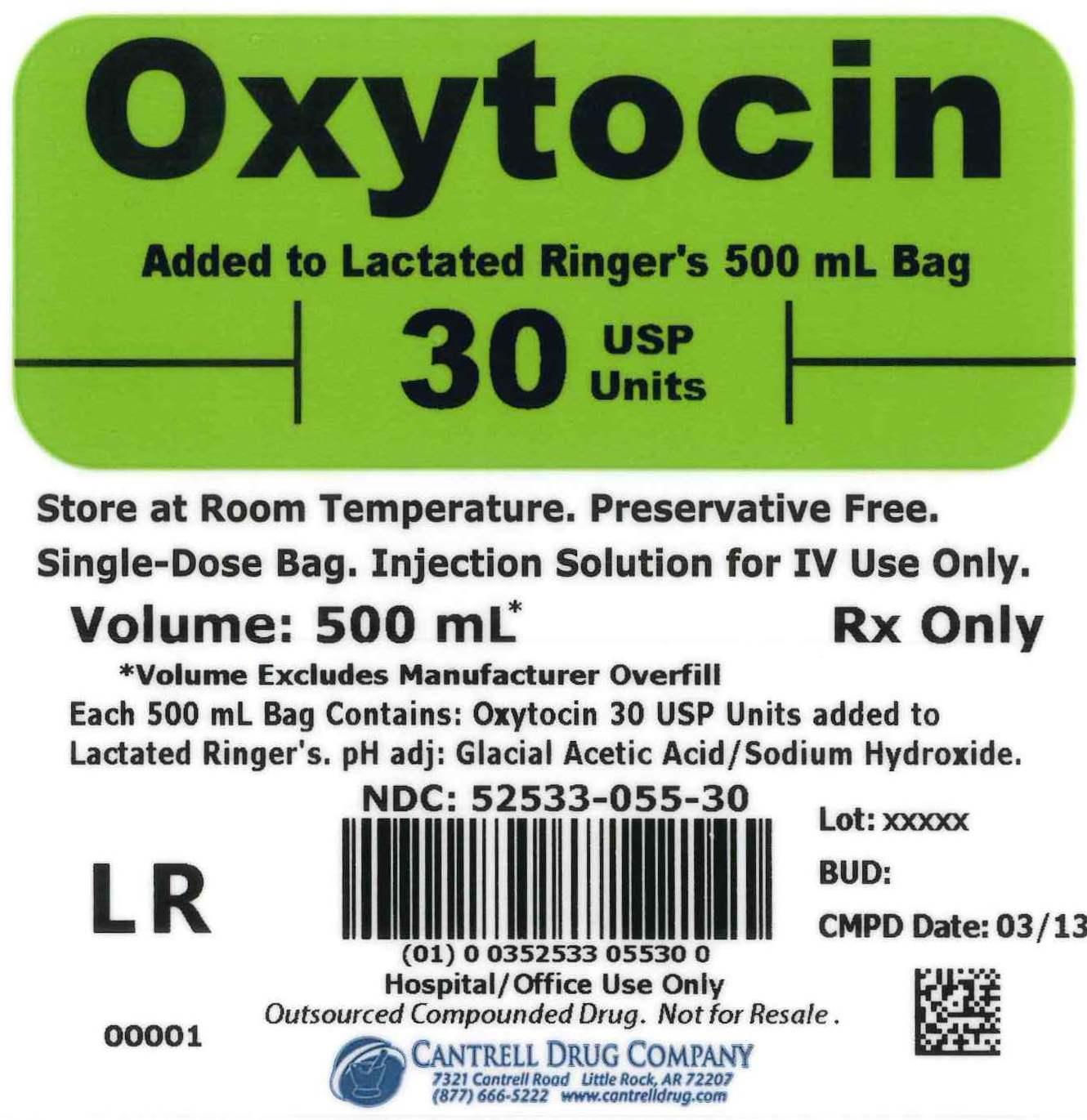 DRUG LABEL: Oxytocin
NDC: 52533-055 | Form: INJECTION, SOLUTION
Manufacturer: Cantrell Drug Company
Category: prescription | Type: HUMAN PRESCRIPTION DRUG LABEL
Date: 20141224

ACTIVE INGREDIENTS: OXYTOCIN 30 [USP'U]/500 mL
INACTIVE INGREDIENTS: SODIUM CHLORIDE 3 g/500 mL; SODIUM LACTATE 1.55 g/500 mL; POTASSIUM CHLORIDE 0.15 g/500 mL; CALCIUM CHLORIDE 0.1 g/500 mL; WATER

Oxytocin 30 USP Units Added to Lactated Ringer's 500 mL Bag